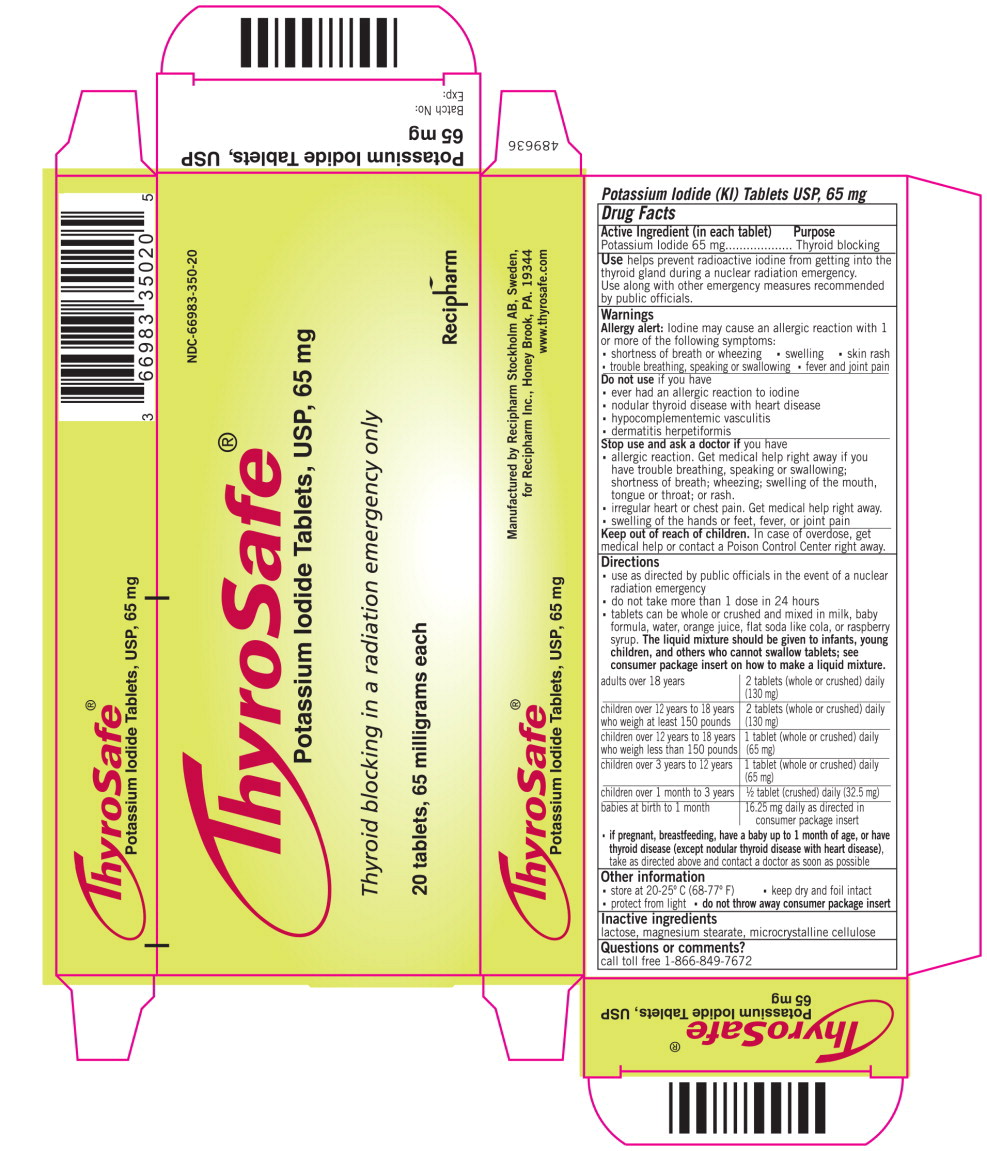 DRUG LABEL: ThyroSafe
NDC: 66983-350 | Form: TABLET
Manufacturer: Recipharm AB (publ)
Category: otc | Type: HUMAN OTC DRUG LABEL
Date: 20211130

ACTIVE INGREDIENTS: Potassium Iodide 65 mg/1 1
INACTIVE INGREDIENTS: Lactose, Unspecified form; Microcrystalline Cellulose; Magnesium Stearate

Drug Facts

Active Ingredient (in each tablet)

Potassium Iodide 65 mg

Purpose

Thyroid blocking

INDICATIONS AND USAGE

Use helps prevent radioactive iodine from getting into the thyroid gland during a nuclear radiation emergency.

Use along with other emergency measures recommended by public officials.

Warnings

Allergy alert: Iodine may cause an allergic reaction with 1 or more of the following symptoms:

- shortness of breath or wheezing
- swelling
- skin rash
- trouble breathing, speaking or swallowing
- fever and joint pain

Do not use if you have

- ever had an allergic reaction to iodine
- nodular thyroid disease with heart disease
- hypocomplementemic vasculitis
- dermatitis herpetiformis

Stop use and ask a doctor if you have

- allergic reaction. Get medical help right away if you have trouble breathing, speaking or swallowing; shortness of breath; wheezing; swelling of the mouth, tongue or throat; or rash.
- irregular heart or chest pain. Get medical help right away.
- swelling of the hands or feet, fever, or joint pain

Keep out of reach of children. In case of overdose, get medical help or contact a Poison Control Center right away.

Directions

- use as directed by public officials in the event of a nuclear radiation emergency
- do not take more than 1 dose in 24 hours
- tablets can be whole or crushed and mixed in milk, baby formula, water, orange juice, flat soda like cola, or raspberry syrup. The liquid mixture should be given to infants, young children, and others who cannot swallow tablets; see consumer package insert on how to make a liquid mixture.

adults over 18 years | 2 tablets (whole or crushed) daily (130 mg)
children over 12 years to 18 years who weigh at least 150 pounds | 2 tablets (whole or crushed) daily (130 mg)
children over 12 years to 18 years who weigh less than 150 pounds | 1 tablet (whole or crushed) daily (65 mg)
children over 3 years to 12 years | 1 tablet (whole or crushed) daily (65 mg)
children over 1 month to 3 years | 1/2 tablet (crushed) daily (32.5 mg)
babies at birth to 1 month | 16.25 mg daily as directed in consumer package insert

PREGNANCY OR BREAST FEEDING

- if pregnant, breastfeeding, have a baby up to 1 month of age, or have thyroid disease (except nodular thyroid disease with heart disease), take as directed above and contact a doctor as soon as possible

Other information

- store at 20-25° C (68-77° F)
- keep dry and foil intact
- protect from light
- do not throw away consumer package insert

Inactive ingredients

lactose, magnesium stearate, microcrystalline cellulose

Questions or comments?

call toll free 1-866-849-7672

Principal Display Panel - 65 mg Carton Label

NDC-66983-350-20

ThyroSafe®

Potassium Iodide Tablets, USP, 65 mg

Thyroid blocking in a radiation emergency only

20 tablets, 65 milligrams each

Recipharm